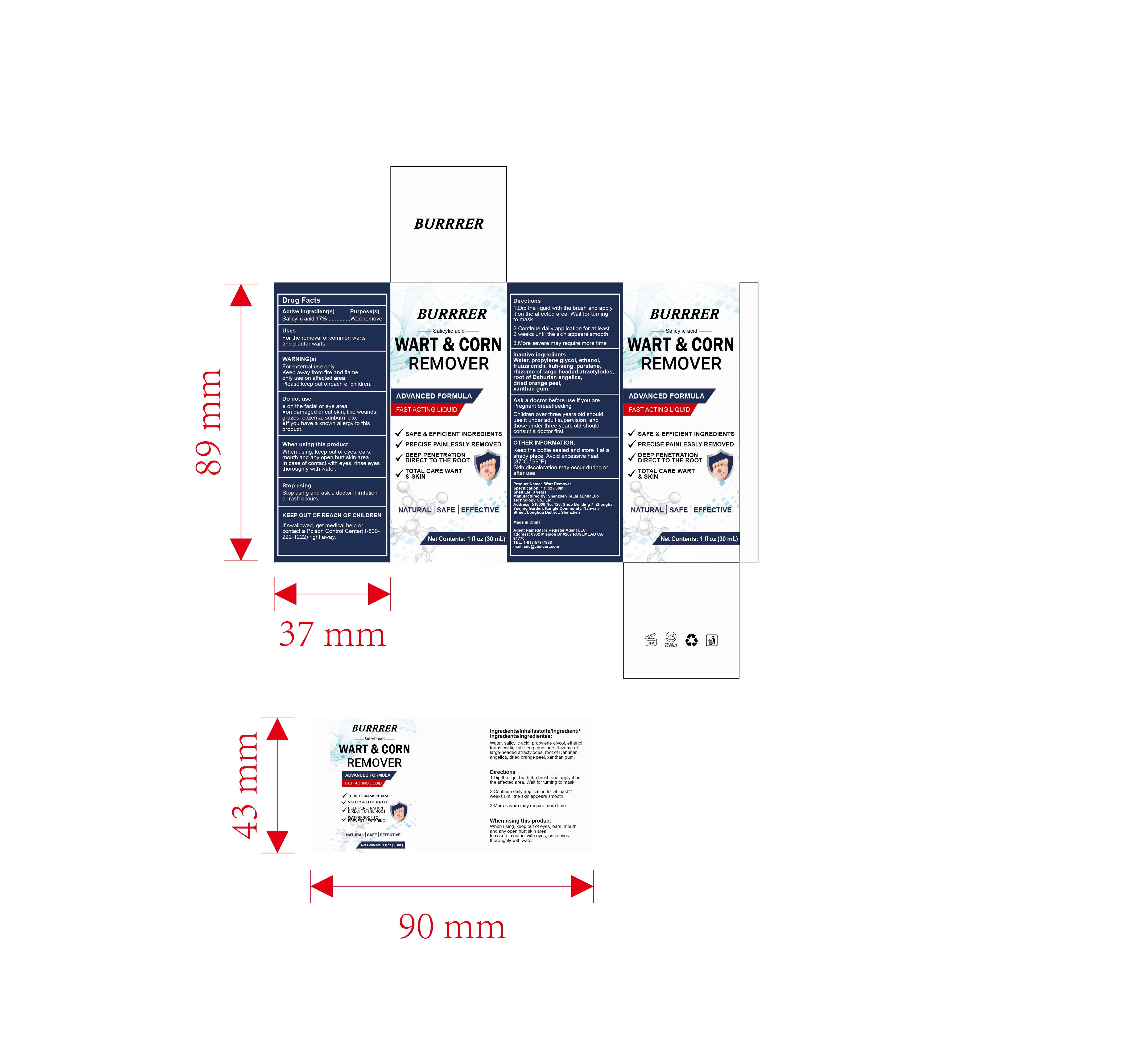 DRUG LABEL: BURRRER Wart Remover
NDC: 85795-001 | Form: LIQUID
Manufacturer: Shenzhen TeLaFaErJiaLuo Technology Co., Ltd.
Category: otc | Type: HUMAN OTC DRUG LABEL
Date: 20250611

ACTIVE INGREDIENTS: SALICYLIC ACID 17 g/100 mL
INACTIVE INGREDIENTS: WATER; ANGELICA DAHURICA ROOT; TANGERINE PEEL; XANTHAN GUM; ACETALDEHYDE; SOPHORA FLAVESCENS ROOT; GLYCOL; CNIDIUM MONNIERI FRUIT; PURSLANE; ATRACTYLODES MACROCEPHALA WHOLE

85795-001

Active Ingredient

salicylic acid 17%

Purpose

WART & CORN REMOVER

Use

For the removal of common warts and plantar warts.

Warnings

For external use only.
Keep away from fire and flame.
only use on affected area.
Please keep outofreach ofchildren.

Do not use

on the facial or eye area.
on damaged or cut skin,like wounds,grazes,eczema,sunburn,etc.
lf you have a known allergy to this product.

When Using

When using,keep out of eyes,ears, mouth and any open hurt skin area.
In case of contact with eyes,rinse eyes thoroughly with water.

Stop Use

Stop using and ask a doctor if irritation or rash occurs.

Ask Doctor

Ask a doctor before use if you are Pregnant breastfeeding
Children over three years old should use it under adult supervision,and those under three years old should
consult a doctor first.

Keep Out Of Reach Of Children

If swallowed,get medical help or contact a Poison Control Center（1-800-222-1222)right away.

Directions

1.Dip the liquid with the brush and apply it on the affected area.Wait for turning to mask.
2.Continue daily application for at least 2 weeks until the skin appears smooth.
3.More severe may require more time

Other information

Keep the bottle sealed and store it at a shady place.Avoid excessive heat (37°℃/99°F).
Skin discoloration may occur during or after use.

Inactive ingredients

Water,propylene glycol,ethanol, frutus cnidii, kuh-seng, purslane, rhizome of large-headed atractylodes, root of Dahurian
angelica, dried orange peel, xanthan gum.